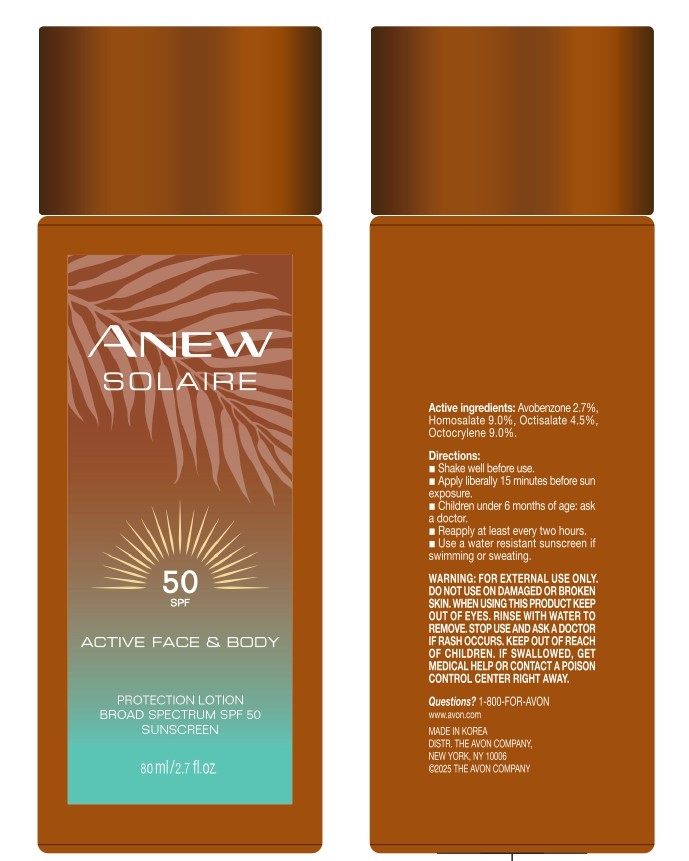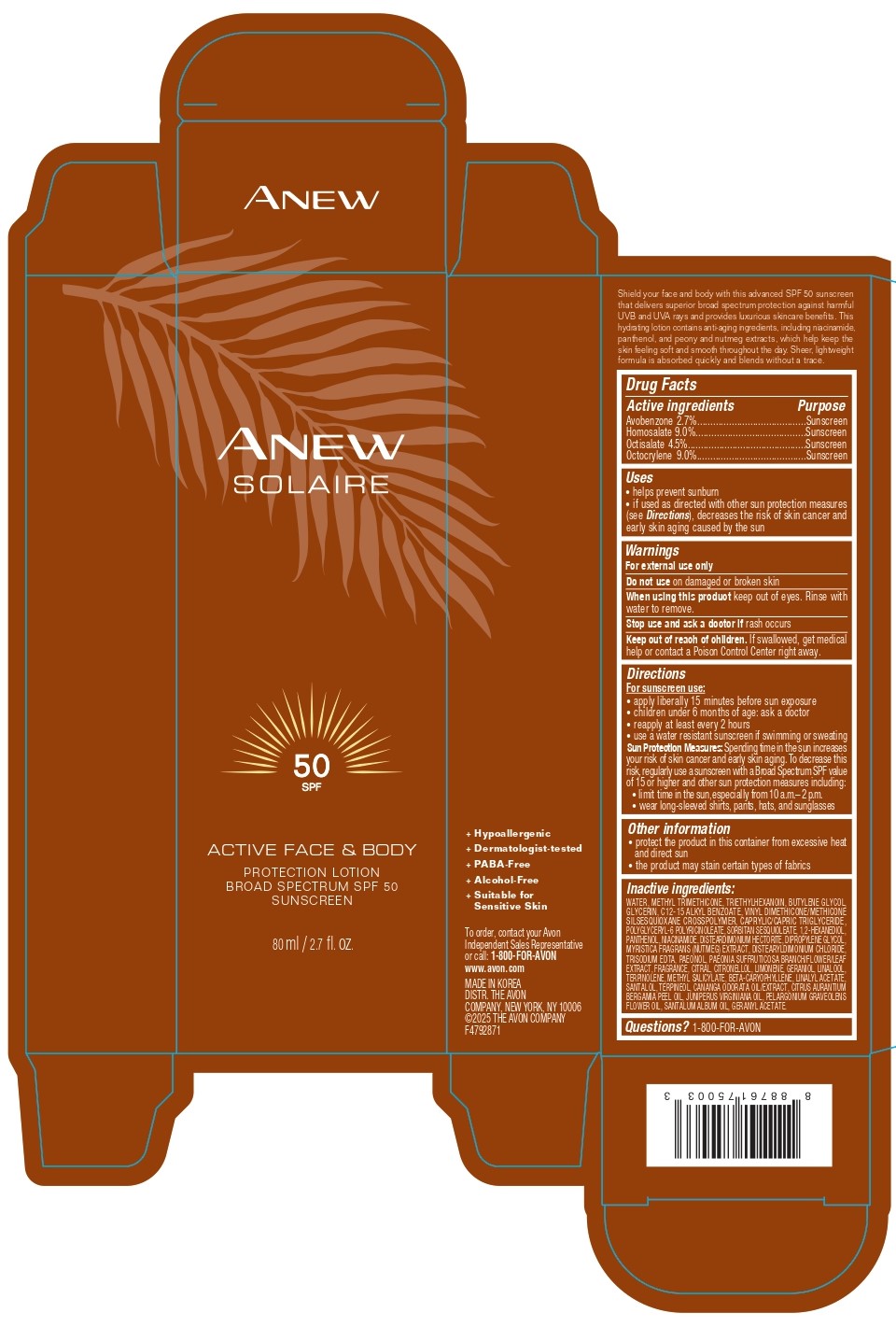 DRUG LABEL: ANEW SOLAIRE ACTIVE FACE AND BODY PROTECTION BROAD SPECTRUM SPF 50 SUNSCREEN
NDC: 10096-2020 | Form: LOTION
Manufacturer: THE AVON COMPANY
Category: otc | Type: HUMAN OTC DRUG LABEL
Date: 20260121

ACTIVE INGREDIENTS: HOMOSALATE 90 mg/1 mL; AVOBENZONE 27 mg/1 mL; OCTOCRYLENE 90 mg/1 mL; OCTISALATE 45 mg/1 mL
INACTIVE INGREDIENTS: 1,2-HEXANEDIOL; CAPRYLIC/CAPRIC TRIGLYCERIDE; DISTEARDIMONIUM HECTORITE; CITRAL; PELARGONIUM GRAVEOLENS FLOWER OIL; TRIETHYLHEXANOIN; SORBITAN SESQUIOLEATE; TRISODIUM EDTA; PANTHENOL; PAEONOL; TERPINOLENE; METHYL SALICYLATE; LINALYL ACETATE; BERGAMOT OIL; BETA-CARYOPHYLLENE; TERPINEOL; DISTEARYLDIMONIUM CHLORIDE; GERANYL ACETATE; GLYCERIN; DIPROPYLENE GLYCOL; NUTMEG; GERANIOL; C12-15 ALKYL BENZOATE; VINYL DIMETHICONE/METHICONE SILSESQUIOXANE CROSSPOLYMER; SANTALOL; CANANGA ODORATA FLOWER OIL; SANTALUM ALBUM (SANDALWOOD) OIL; METHYL TRIMETHICONE; LINALOOL; WATER; NIACINAMIDE; CITRONELLOL; JUNIPERUS VIRGINIANA OIL; BUTYLENE GLYCOL; POLYGLYCERYL-6 RICINOLEATE; LIMONENE, (+)-

ANEW SOLAIRE ACTIVE FACE AND BODY PROTECTION LOTION BROAD SPECTRUM SPF 50

ACTIVE INGREDIENTS

AVOBENZONE 2.7%

HOMOSALATE 9.0%

OCTISALATE 4.5%

OCTOCRYLENE 9.0%

Purpose

Sunscreen

Uses

- helps prevent sunburn
- if used as directed with other sun protection measures (see Directions), decreases the risk of skin cancer and early skin aging caused by the sun

Warnings

For external use only

Do not use on damaged or broken skin

When using

When using this product keep out of eyes. Rinse with water to remove.

Stop use and ask a doctor if rash occurs

Keep out of reach of children

DOSAGE AND ADMINISTRATION

If swallowed, get medical help or contact a Poison Control Center right away.

Directions

For sunscreen use:

- apply liberally 15 minutes before sun exposure
- children under 6 months of age: ask a doctor
- reapply at least every 2 hours
- use a water resistant sunscreen if swimming or sweating

Sun Protection Measures: Spending time in the sun increases your risk of skin cancer and early skin aging. To decrease this risk, regularly use a sunscreen with a Broad Spectrum SPF value of 15 or higher and other sun protection measures including:

- limit time in the sun, especially from 10 a.m. - 2 p.m.
- wear long-sleeved shirts, pants, hats, and sunglasses

Other information

- protect the product in this container from excessive heat and direct sun
- the product may stain certain types of fabrics

Inactive ingredients:

WATER, METHYL TRIMETHICONE, TRIETHYLHEXANOIN, BUTYLENE GLYCOL, GLYCERIN, C12-15 ALKYL BENZOATE, VINYL DIMETHICONE/METHICONE SILSESQUIOXANE CROSSPOLYMER, CAPRYLIC/CAPRIC TRIGLYCERIDE, POLYGLYCERYL-6 POLYRICINOLEATE, SORBITAN SESQUIOLEATE, 1,2-HEXANEDIOL, PANTHENOL, NIACINAMIDE, DISTEARDIMONIUM HECTORITE, DIPROPYLENE GLYCOL, MYRISTICA FRAGRANS (NUTMEG) EXTRACT, DISTEARYLDIMONIUM CHLORIDE, TRISODIUM EDTA, PAEONOL, PAEONIA SUFFRUTICOSA BRANCH/FLOWER/LEAF EXTRACT, FRAGRANCE, CITRAL, CITRONELLOL, LIMONENE, GERANIOL, LINALOOL, TERPINOLENE, METHYL SALICYLATE, BETA-CARYOPHYLLENE, LINALYL ACETATE, SANTALOL, TERPINEOL, CANANGA ODORATA OIL/EXTRACT, CITRUS AURANTIUM BERGAMIA PEEL OIL, JUNIPERUS VIRGINIANA OIL, PELARGONIUM GRAVEOLENS FLOWER OIL, SANTALUM ALBUM OIL, GERANYL ACETATE.

Questions?

1-800-FOR-AVON